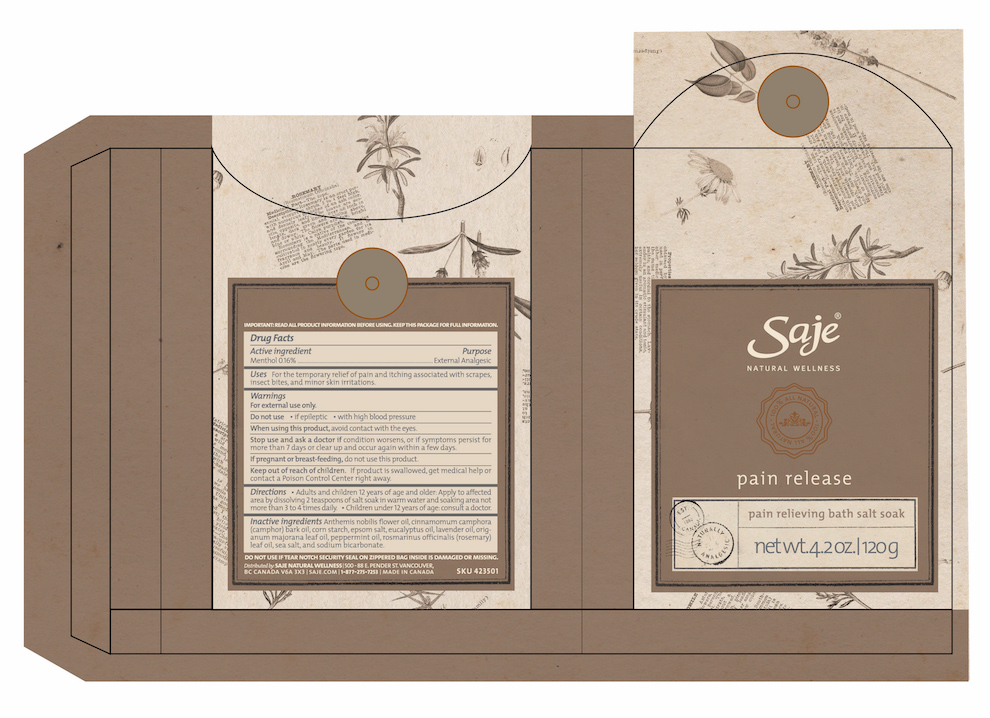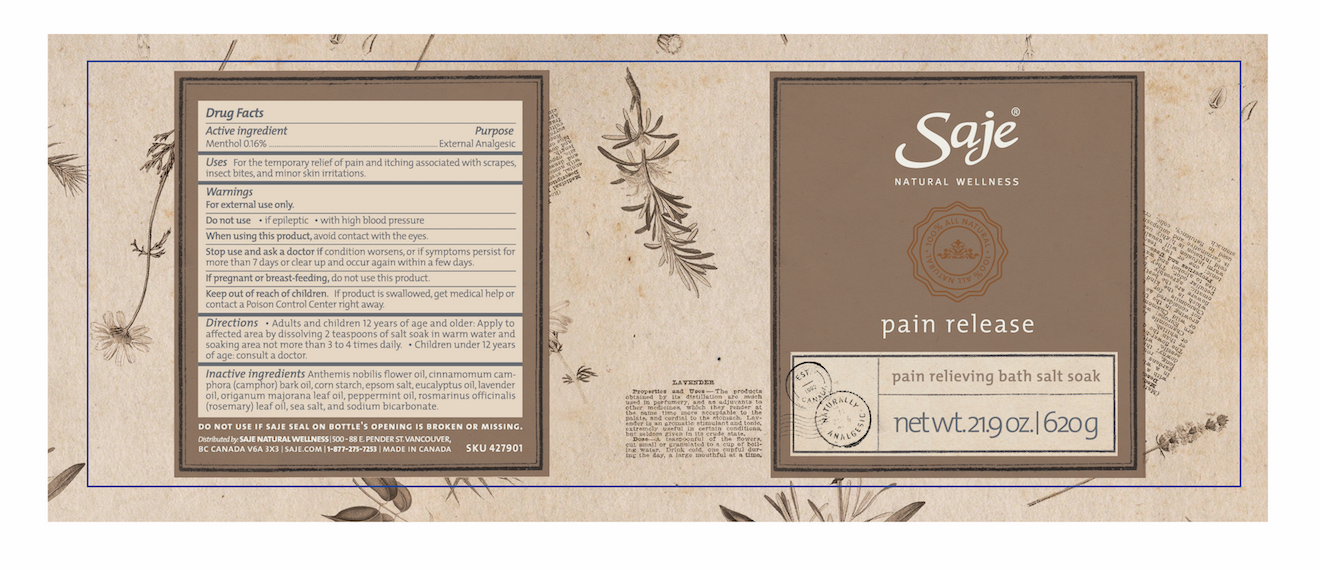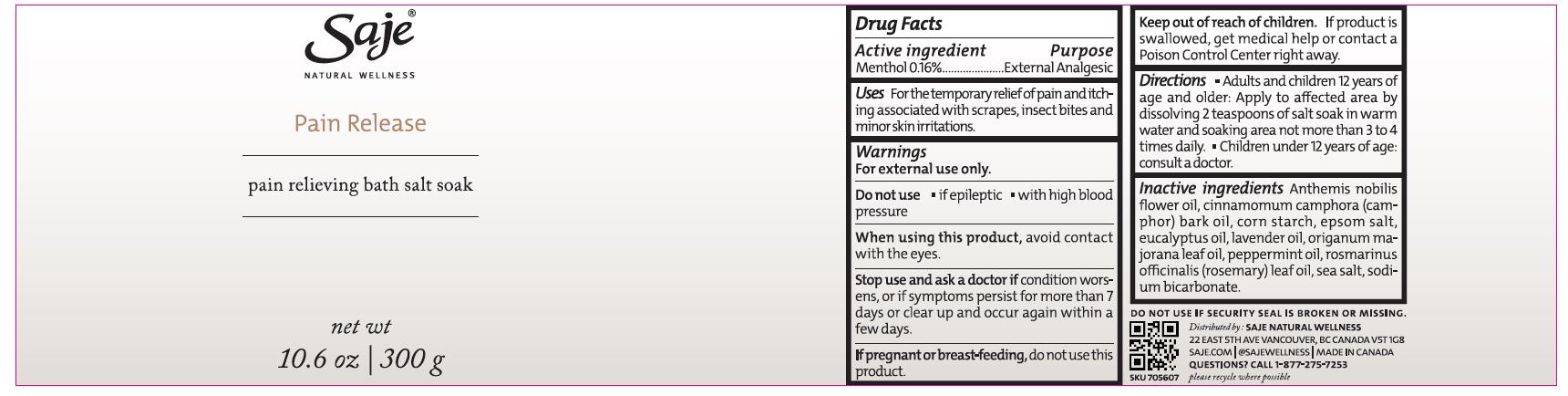 DRUG LABEL: Pain Release
NDC: 70983-004 | Form: GRANULE
Manufacturer: Saje Natural Business Inc.
Category: otc | Type: HUMAN OTC DRUG LABEL
Date: 20260113

ACTIVE INGREDIENTS: MENTHOL 1.6 mg/1 g
INACTIVE INGREDIENTS: CHAMAEMELUM NOBILE FLOWER OIL; CAMPHOR OIL; STARCH, CORN; MAGNESIUM SULFATE HEPTAHYDRATE; EUCALYPTUS OIL; LAVENDER OIL; SWEET MARJORAM OIL; PEPPERMINT OIL; ROSEMARY OIL; SEA SALT; SODIUM BICARBONATE

Pain Release Bath Salt Soak

DRUG FACTS Active ingredient

Menthol 0.16%

Purpose External Analgesic

Uses For the temporary relief of pain and itching associated with scrapes, insect bites, and minor skin irritations.

Warnings

For external use only.

Do not use

- if epileptic
- with high blood pressure

When using this product,

avoid contact with the eyes.

Stop use and ask a doctor if

condition worsens, or if symptoms persist for more than 7 days or clear up and occur again within a few days.

If pregnant or breast-feeding,

do not use this product.

Keep out of reach of children.

If product is swallowed, get medical help or contact a Poison Control Center right away.

Directions

- Adults and children 12 years of age and older: Apply to affected area by dissolving 2 teaspoons of salt soak in warm water and soaking area

DOSAGE AND ADMINISTRATION

not more than 3 to 4 times daily.

- Children under 12 years of age: consult a doctor.

Inactive ingredients

Anthemis nobilis flower oil, cinnamomum camphora (camphor) bark oil, corn starch, epsom salt, eucalyptus oil, lavender oil, origanum majorana leaf oil, peppermint oil, rosmarinus officinalis (rosemary) leaf oil, sea salt, and sodium bicarbonate.

QUESTIONS

Distributed by: SAJE NATURAL WELLNESS 500-88 E. Pender St. Vancouver, BC Canada V6A 3X3 | saje.com | 1-877-275-7253 | Made in Canada

Pain Release 620 g

DO NOT USE IF SAJE SEAL ON BOTTLE'S OPENING IS BROKEN OR MISSING.

SKU 427901

Pain Release 120 g

DO NOT USE IF TEAR NOTCH SECURITY SEAL ON ZIPPERED BAG INSIDE IS DAMAGED OR MISSING

SKU 423501

Pain Release Bath Salt Soak 120 g

Saje Natural Wellness

Pain Release

Pain Relieving Bath Salt Soak

net wt. 4.2 oz. | 120 g

Pain Release Bath Salt Soak 620 g

Saje® Natural Wellness

Pain Release

Pain Relieving Bath Salt Soak

net wt. 21.9 oz. | 620 g

Pain Release Pain Relieving Bath Salt Soak net wt. 10.6 oz. | 300 g

Saje Natural Wellness

Pain Release

Pain Relieving Bath Salt Soak

net wt. 10.6 oz. | 300 g